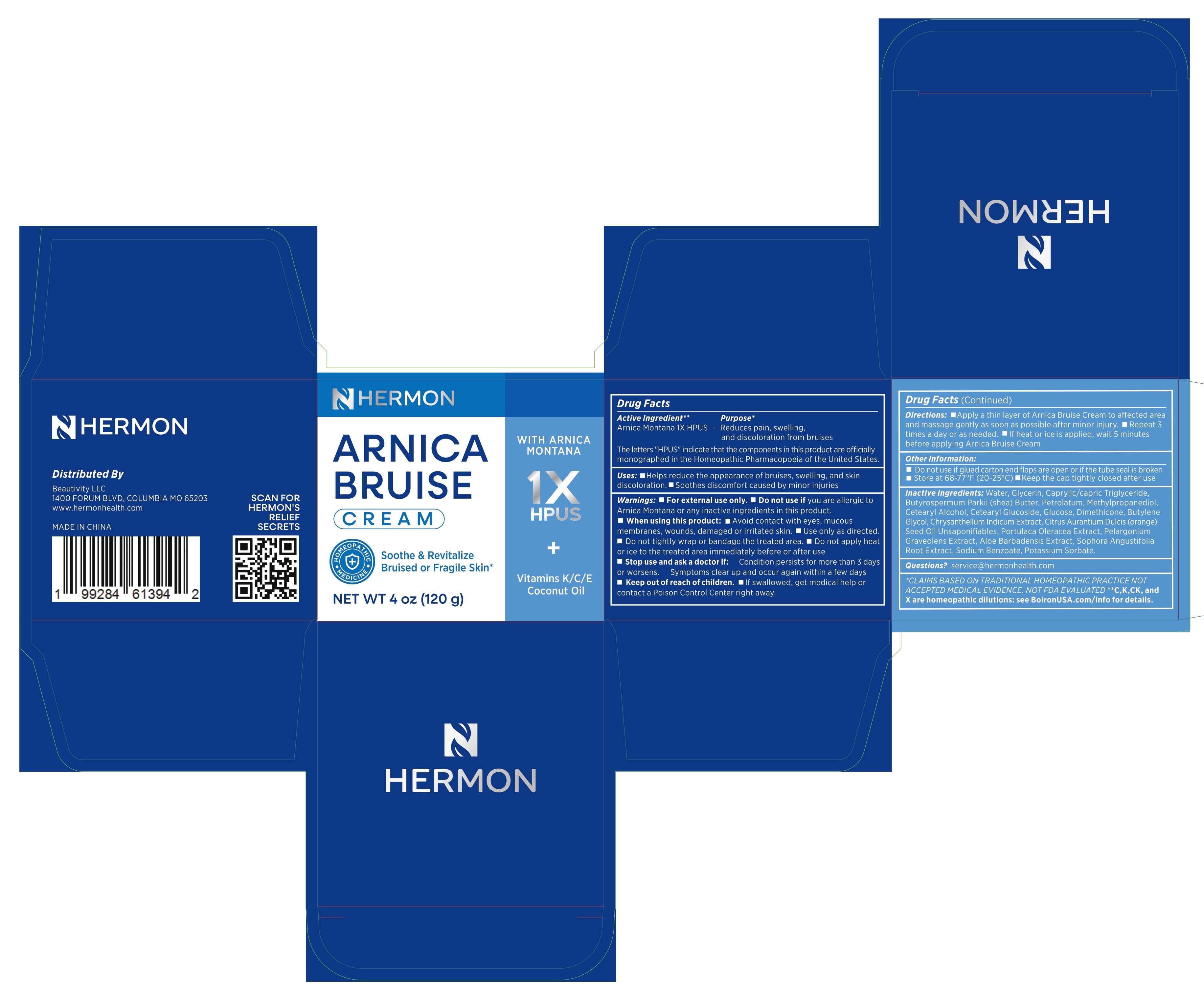 DRUG LABEL: Arnica Bruise Cream
NDC: 85398-005 | Form: CREAM
Manufacturer: Beautivity LLC
Category: homeopathic | Type: HUMAN OTC DRUG LABEL
Date: 20260302

ACTIVE INGREDIENTS: ARNICA MONTANA 1 [hp_X]/1 1
INACTIVE INGREDIENTS: GLUCOSE; POTASSIUM SORBATE; PORTULACA OLERACEA WHOLE; BUTYROSPERMUM PARKII (SHEA) BUTTER; CETEARYL ALCOHOL; BUTYLENE GLYCOL; PELARGONIUM GRAVEOLENS WHOLE; SODIUM BENZOATE; CETEARYL GLUCOSIDE; CHRYSANTHEMUM INDICUM WHOLE; DIMETHICONE; CITRUS AURANTIUM DULCIS (ORANGE) SEED OIL; METHYLPROPANEDIOL; CAPRYLIC/CAPRIC TRIGLYCERIDE; ALOE BARBADENSIS LEAF; PETROLATUM; WATER; GLYCERIN

Update-85398-005-01

ACTIVE INGREDIENT

Arnica Montana 1X HPUS
The letters “HPUS” indicate that the components in this product are officially monographed in the Homeopathic Pharmacopoeia of the United States.

PURPOSE

Reduces pain, swelling, and discoloration from bruises

INDICATIONS AND USAGE

- Helps reduce the appearance of bruises, swelling, and skin discoloration.
- Soothes discomfort caused by minor injuries

WARNINGS

For external use only.

DO NOT USE

if you are allergic to Arnica Montana or any inactive ingredients in this product.

WHEN USING

- Avoid contact with eyes, mucous membranes, wounds, damaged or irritated skin.
- Use only as directed.
- Do not tightly wrap or bandage the treated area.
- Do not apply heat or ice to the treated area immediately before or after use.

Stop use and ask a doctor if:

- Condition persists for more than 3 days or worsens.
- Symptoms clear up and occur again within a few days

KEEP OUT OF REACH OF CHILDREN

If swallowed, get medical help or contact a Poison Control Center right away.

DOSAGE AND ADMINISTRATION

- Apply a thin layer of Arnica Bruise Cream to affected area and massage gently as soon as possible after minor injury.
- Repeat 3 times a day or as needed.
- If heat or ice is applied, wait 5 minutes before applying Arnica Bruise Cream

- Do not use if glued carton end flaps are open or if the tube seal is broken
- Store at 68-77°F (20-25°C)
- Keep the cap tightly closed after use

INACTIVE INGREDIENT

Water, Glycerin, Caprylic/capric Triglyceride, Butyrospermum Parkii (Shea) Butter, Petrolatum, Methylpropanediol, Cetearyl Alcohol, Cetearyl Glucoside, Glucose, Dimethicone, Butylene Glycol, Chrysanthellum Indicum Extract, Citrus Aurantium Dulcis (Orange) Seed Oil Unsaponifiables, Portulaca Oleracea Extract, Pelargonium Graveolens Extract, Aloe Barbadensis Extract, Sodium Benzoate, Potassium Sorbate.

QUESTIONS

service@hermonhealth.com